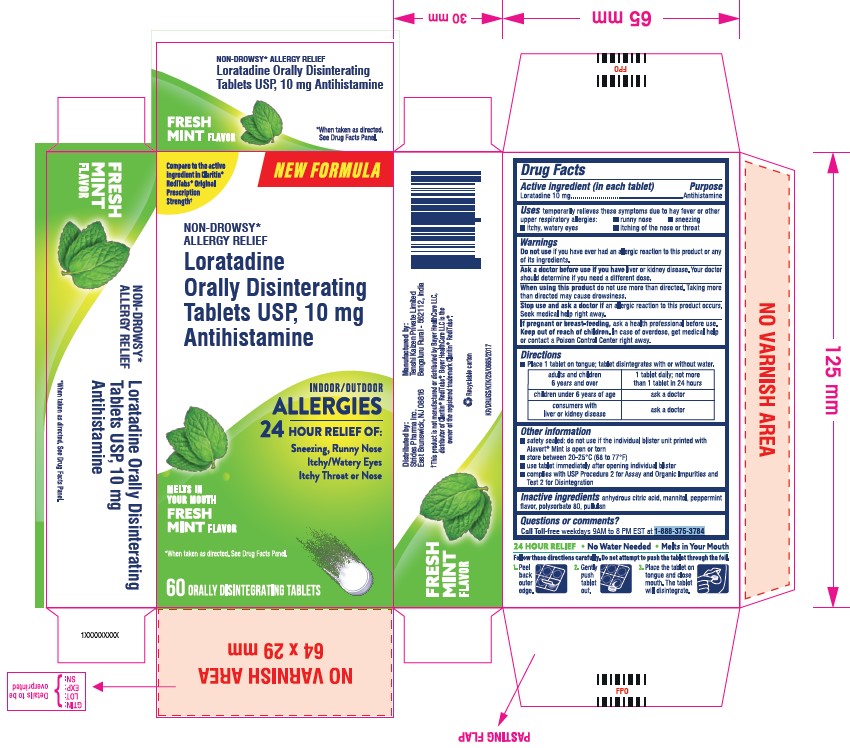 DRUG LABEL: LORATADINE
NDC: 72983-503 | Form: TABLET, ORALLY DISINTEGRATING
Manufacturer: Tenshi Kaizen Pvt Ltd
Category: otc | Type: HUMAN OTC DRUG LABEL
Date: 20240507

ACTIVE INGREDIENTS: LORATADINE 10 mg/1 1
INACTIVE INGREDIENTS: ANHYDROUS CITRIC ACID; POLYSORBATE 80; MANNITOL; PULLULAN

Loratidine Orally Disintegrating Tablets, USP
Mint Flavor

Drug Facts

Active ingredient (in each tablet)

Loratadine 10 mg

Purpose

Antihistamine

Uses

temporarily relieves these symptoms due to hay fever or other upper respiratory allergies:

- runny nose
- sneezing
- itchy, watery eyes
- itching of the nose or throat

Warnings

DO NOT USE

Do not useif you have ever had an allergic reaction to this product or any of its ingredients

Ask a doctor before use if you haveliver or kidney disease. Your doctor should determine if you need a different dose.

WHEN USING

When using this productdo not use more than directed. Taking more than recommended may cause drowsiness.

Stop use and ask a doctor ifan allergic reaction to this product occurs. Seek medical help right away.

PREGNANCY OR BREAST FEEDING

If pregnant or breast-feeding,ask a health professional before use.

Keep out of reach of children.In case of overdose, get medical help or contact a Poison Control Center right away.

Directions

- Place 1 tablet on tongue; tablet disentigrates with or without water.

adults and children 6 years and over | 1 tablet daily; do not use more than 1 tablet in 24 hours
children under 6 years of age | ask a doctor
consumers who have liver or kidney disease | ask a doctor

Other information

- safety sealed: do not use if the individual blister unit printed with Loratadine orally disintegrating tablet is open or torn
- store at 20-25°C (68-77°F)
- use tablet immediately after opening individual blister
- complies with USP Procedure 2 for Assay and Organic Impurities and Test 2 for Disintegration

Inactive ingredients

anhydrous citric acid, mannitol, peppermint flavor, polysorbate 80, pullulan

Questions or comments?

Call Toll-free weekdays 9 AM to 5 PM EST at 1-888-375-3784

Manufactured By: Tenshi Kaizen Private Limited

Bengaluru Rural - 562112, India

PRINCIPAL DISPLAY PANEL - 10 mg Tablet Blister Pack Carton

NEW FORMULA

NON-DROWSY*

ALLERGY RELIEF

Loratadine Orally Disintegrating Tablet USP, 10 mg
Antihistamine

Indoor/Outdoor

ALLERGIES

24 Hour Relief of

Sneezing, Runny Nose

Itchy/Watery Eyes

Itchy Throat or Nose

Melts In Your Mouth

FRESH MINT Flavor

*When taken as directed. See Drug Facts Panel.

60 Orally Disintegrating Tablets